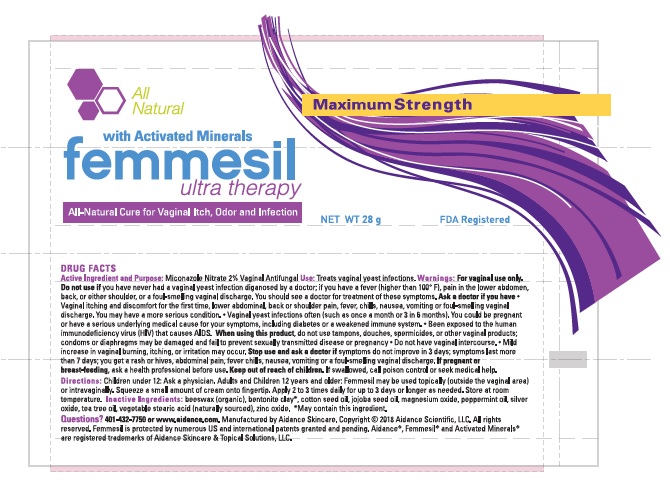 DRUG LABEL: Femmesil
NDC: 24909-202 | Form: OINTMENT
Manufacturer: Aidance Skincare & Topical Solutions, LLC
Category: otc | Type: HUMAN OTC DRUG LABEL
Date: 20250825

ACTIVE INGREDIENTS: MICONAZOLE NITRATE 2 g/100 g
INACTIVE INGREDIENTS: COTTONSEED OIL; JOJOBA OIL; MAGNESIUM OXIDE; PEPPERMINT OIL; SILVER OXIDE; STEARIC ACID; TEA TREE OIL; WHITE WAX; ZINC OXIDE

24909-202 femmesil

Active Ingredient

Miconazole Nitrate 2%.

Purpose

Vaginal Antifungal.

Use.

Treats vaginal yeast infections

Warnings

For vaginal use only. Do not useif you have never had a vaginal yeast infection diagnosed by a doctor; if you have a fever (higher than 100° F), pain in the lower abdomen, back, or either shoulder, or a foul-smelling vaginal discharge. You should see a doctor for treatment of these symptoms.

Ask doctor before use if you have

- Vaginal itching and discomfort for the first time; lower abdominal, back or shoulder pain, fever, chills, nausea, vomiting or foul-smelling vaginal discharge. You may have a more serious condition.

- Vaginal yeast infections often (such as once a month or 3 in 6 months). You could be pregnant or have a serious underlying medical cause for your symptoms, including diabetes or a weakened immune system.

- Been exposed to the human immunodeficiency virus (HIV) that causes AIDS.

When using this product

- Do not use tampons, douches, spermicides, or other vaginal products; condoms or diaphragms may be damaged and fail to prevent sexually transmitted disease or pregnancy.
- Do not have vaginal intercourse.
- Mild increase in vaginal burning, itching or irritation may occur.

Stop use and ask a doctor ifsymptoms do not get better in 3 days; symptoms last more than 7 days; you get a rash orhives, abdominal pain, fever, chills, nausea, vomiting or a foul-smelling vaginal discharge.

Directions

Children under 12 | Ask a physician
Adults and children 12 years and over | Femmesil may be used topically (outside the vaginal area) or intravaginally. Squeeze a small amount of cream onto fingertip. Apply 2-3 times daily for up to 3 days or longer, as needed.

PREGNANCY OR BREAST FEEDING

If pregnant or breast-feeding,ask a health professional before use.

Keep out of reach of children.

If swallowed, call poison control or seek medical help

Other Information

Store at room temperature

Inactive Ingredients

beeswax (organic), bentonite clay, cotton seed oil, jojoba seed oil, magnesium oxide, peppermint oil, silver oxide, stearic acid, tea tree oil, zinc oxide.

Questions?877-4-AIDANCE